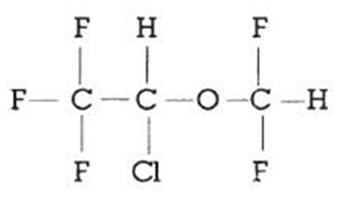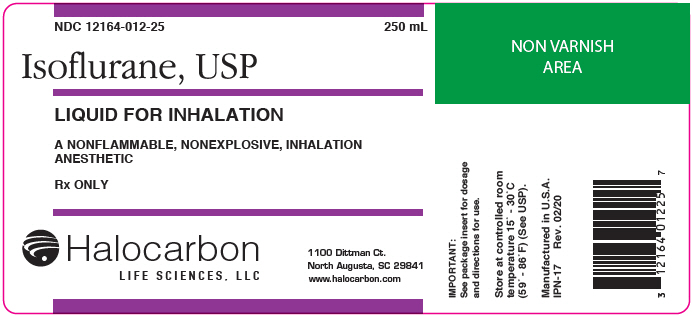 DRUG LABEL: Isoflurane
NDC: 12164-012 | Form: LIQUID
Manufacturer: Halocarbon Life Sciences, LLC
Category: prescription | Type: HUMAN PRESCRIPTION DRUG LABEL
Date: 20240913

ACTIVE INGREDIENTS: Isoflurane 1 mL/1 mL

Isoflurane, USP
Liquid For Inhalation

Rx only

DESCRIPTION

Isoflurane, USP, a nonflammable liquid administered by vaporizing, is a general inhalation anesthetic drug. It is 1-chloro-2,2,2-trifluoroethyl difluoromethyl ether, and its structural formula is:

Some physical constants are:

Molecular weight |  | 184.5
Boiling point at 760 mm Hg |  | 48.5°C (uncorr.)
Refractive index n^20D |  | 1.2990-1.3005
Specific gravity 25° / 25°C |  | 1.496
Vapor pressure in mm Hg [Equation for vapor pressure calculation:] | 20°C | 238
 | 25ºC | 295
 | 30°C | 367
 | 35°C | 450

Log10Pvap = | A + B T | where: | A=8.056 B=-1664.58 T=°C = 273.16 (Kelvin

Partition coefficients at 37°C:

Water / gas |  | 0.61
Blood / gas |  | 1.43
Oil / gas |  | 90.8

Partition coefficients at 25°C - rubber and plastic

Conductive rubber / gas |  | 62.0
Butyl rubber / gas |  | 75.0
Polyvinyl chloride / gas |  | 110.0
Polyethylene / gas |  | ~2.0
Polyurethane / gas |  | ~1.4
Polyolefin / gas |  | ~1.1
Butyl acetate / gas |  | ~2.5

Purity by gas chromatography |  | >99.9%

Lower limit of flammability in oxygen or nitrous oxide at 9 joules/sec. and 23ºC |  | None

Lower limit of flammability in oxygen or nitrous oxide at 900 joules/sec. and 23ºC |  | Greater than useful concentration in anesthesia

Isoflurane is a clear, colorless, stable liquid containing no additives or chemical stabilizers. Isoflurane has a mildly pungent, musty, ethereal odor. Samples stored in indirect sunlight in clear, colorless glass for five years, as well as samples directly exposed for 30 hours to a 2 amp, 115 volt, 60 cycle long wave U.V. light were unchanged in composition as determined by gas chromatography. Isoflurane in one normal sodium methoxide-methanol solution, a strong base, for over six months consumed essentially no alkali, indicative of strong base stability. Isoflurane does not decompose in the presence of soda lime (at normal operating temperatures), and does not attack aluminum, tin, brass, iron, or copper.

CLINICAL PHARMACOLOGY

Isoflurane is an inhalation anesthetic. The MAC (minimum alveolar concentration) in man is as follows:

 | Age | 100% Oxygen | 70% N2O
 | 26 ± 4 | 1.28 | 0.56
 | 44 ± 7 | 1.15 | 0.50
 | 64 ± 5 | 1.05 | 0.37

Induction of and recovery from isoflurane anesthesia are rapid. Isoflurane has a mild pungency which limits the rate of induction, although excessive salivation or tracheobronchial secretions do not appear to be stimulated. Pharyngeal and laryngeal reflexes are readily obtunded. The level of anesthesia may be changed rapidly with isoflurane. Isoflurane is a profound respiratory depressant. RESPIRATION MUST BE MONITORED CLOSELY AND SUPPORTED WHEN NECESSARY. As anesthetic dose is increased, tidal volume decreases and respiratory rate is unchanged. This depression is partially reversed by surgical stimulation, even at deeper levels of anesthesia. Isoflurane evokes a sigh response reminiscent of that seen with diethyl ether and enflurane, although the frequency is less than with enflurane.

Blood pressure decreases with induction of anesthesia but returns toward normal with surgical stimulation. Progressive increases in depth of anesthesia produce corresponding decreases in blood pressure. Nitrous oxide diminishes the inspiratory concentration of isoflurane required to reach a desired level of anesthesia and may reduce the arterial hypotension seen with isoflurane alone. Heart rhythm is remarkably stable. With controlled ventilation and normal PaCO2, cardiac output is maintained despite increasing depth of anesthesia primarily through an increase in heart rate which compensates for a reduction in stroke volume. The hypercapnia which attends spontaneous ventilation during isoflurane anesthesia further increases heart rate and raises cardiac output above awake levels. Isoflurane does not sensitize the myocardium to exogenously administered epinephrine in the dog. Limited data indicate that subcutaneous injection of 0.25mg of epinephrine (50 mL of 1:200,000 solution) does not produce an increase in ventricular arrhythmias in patients anesthetized with isoflurane.

Muscle relaxation is often adequate for intra-abdominal operations at normal levels of anesthesia. Complete muscle paralysis can be attained with small doses of muscle relaxants. ALL COMMONLY USED MUSCLE RELAXANTS ARE MARKEDLY POTENTIATED WITH ISOFLURANE, THE EFFECT BEING MOST PROFOUND WITH THE NONDEPOLARIZING TYPE. Neostigmine reverses the effect of nondepolarizing muscle relaxants in the presence of isoflurane. All commonly used muscle relaxants are compatible with isoflurane.

Isoflurane can produce coronary vasodilation at the arteriolar level in selected animal models; the drug is probably also a coronary dilator in humans. Isoflurane, like some other coronary arteriolar dilators, has been shown to divert blood from collateral dependent myocardium to normally perfused areas in an animal model ("coronary steal"). Clinical studies to date evaluating myocardial ischemia, infarction and death as outcome parameters have not established that the coronary arteriolar dilation property of isoflurane is associated with coronary steal or myocardial ischemia in patients with coronary artery disease.

Pharmacokinetics

Isoflurane undergoes minimal biotransformation in man. In the postanesthesia period, only 0.17% of the isoflurane taken up can be recovered as urinary metabolites.

INDICATIONS AND USAGE

Isoflurane may be used for induction and maintenance of general anesthesia. Adequate data have not been developed to establish its application in obstetrical anesthesia.

CONTRAINDICATIONS

Known sensitivity to isoflurane, or to other halogenated agents.

Known or suspected genetic susceptibility to malignant hyperthermia.

WARNINGS

Perioperative Hyperkalemia

Use of inhaled anesthetic agents has been associated with rare increases in serum potassium levels that have resulted in cardiac arrhythmias and death in pediatric patients during the postoperative period. Patients with latent as well as overt neuromuscular disease, particularly Duchenne muscular dystrophy, appear to be most vulnerable. Concomitant use of succinylcholine has been associated with most, but not all, of these cases. These patients also experienced significant elevations in serum creatinine kinase levels and, in some cases, changes in urine consistent with myoglobinuria. Despite the similarity in presentation to malignant hyperthermia, none of these patients exhibited signs or symptoms of muscle rigidity or hypermetabolic state. Early and aggressive intervention to treat the hyperkalemia and resistant arrhythmias is recommended, as is subsequent evaluation for latent neuromuscular disease.

Malignant Hyperthermia

In susceptible individuals, isoflurane anesthesia may trigger a skeletal muscle hypermetabolic state leading to high oxygen demand and the clinical syndrome known as malignant hyperthermia. The syndrome includes nonspecific features such as muscle rigidity, tachycardia, tachypnea, cyanosis, arrhythmias and unstable blood pressure. (It should also be noted that many of these nonspecific signs may appear with light anesthesia, acute hypoxia, etc.) An increase in overall metabolism may be reflected in an elevated temperature (which may rise rapidly early or late in the case, but usually is not the first sign of augmented metabolism) and an increased usage of the CO2 absorption system (hot cannister). PaO2 and pH may decrease, and hyperkalemia and a base deficit may appear. Treatment includes discontinuance of triggering agents (e.g., isoflurane), administration of intravenous dantrolene sodium, and application of supportive therapy. Such therapy includes vigorous efforts to restore body temperature to normal, respiratory and circulatory support as indicated, and management of electrolyte- fluid-acid-base derangements. (Consult prescribing information for dantrolene sodium intravenous for additional information on patient management). Renal failure may appear later, and urine flow should be sustained if possible.

Since levels of anesthesia may be altered easily and rapidly, only vaporizers producing predictable concentrations should be used Hypotension and respiratory depression increase as anesthesia is deepened.

Increased blood loss comparable to that seen with halothane has been observed in patients undergoing abortions.

Isoflurane markedly increases cerebral blood flow at deeper levels of anesthesia. There may be a transient rise in cerebral spinal fluid pressure which is fully reversible with hyperventilation.

Pediatric Neurotoxicity

Published animal studies demonstrate that the administration of anesthetic and sedation drugs that block NMDA receptors and/or potentiate GABA activity increase neuronal apoptosis in the developing brain and result in long-term cognitive deficits when used for longer than 3 hours. The clinical significance of these findings is not clear. However, based on the available data, the window of vulnerability to these changes is believed to correlate with exposures in the third trimester of gestation through the first several months of life, but may extend out to approximately three years of age in humans (See PRECAUTIONS/ Pregnancy, Pediatric Use, and ANIMAL TOXICOLOGY AND/OR PHARMACOLOGY).

Some published studies in children suggest that similar deficits may occur after repeated or prolonged exposures to anesthetic agents early in life and may result in adverse cognitive or behavioral effects. These studies have substantial limitations, and it is not clear if the observed effects are due to the anesthetic/sedation drug administration or other factors such as the surgery or underlying illness.

Anesthetic and sedation drugs are a necessary part of the care of children and pregnant women needing surgery, other procedures, or tests that cannot be delayed, and no specific medications have been shown to be safer than any other. Decisions regarding the timing of any elective procedures requiring anesthesia should take into consideration the benefits of the procedure weighed against the potential risks.

PRECAUTIONS

General

As with any potent general anesthetic isoflurane should only be administered in an adequately equipped anesthetizing environment by those who are familiar with the pharmacology of the drug and qualified by training and experience to manage the anesthetized patient.

Regardless of the anesthetics employed, maintenance of normal hemodynamics is important to the avoidance of myocardial ischemia in patients with coronary artery disease

Isoflurane, like some other inhalational anesthetics, can react with desiccated carbon dioxide (CO2) absorbents to produce carbon monoxide which may result in elevated levels of carboxyhemoglobin in some patients. Case reports suggest that barium hydroxide lime and soda lime become desiccated when fresh gases are passed through the CO2 absorber cannister at high flow rates over many hours or days. When a clinician suspects that CO2 absorbent may be desiccated, it should be replaced before the administration of isoflurane.

As with other halogenated anesthetic agents, isoflurane may cause sensitivity hepatitis in patients who have been sensitized by previous exposure to halogenated anesthetics (see CONTRAINDICATIONS).

Information for Patients

Isoflurane, as well as other general anesthetics, may cause a slight decrease in intellectual function for 2 or 3 days following anesthesia. As with other anesthetics, small changes in moods and symptoms may persist for up to 6 days after administration.

Effect of anesthetic and sedation drugs on early brain development

Studies conducted in young animals and children suggest repeated or prolonged use of general anesthetic or sedation drugs in children younger than 3 years may have negative effects on their developing brains. Discuss with parents and caregivers the benefits, risks, and timing and duration of surgery or procedures requiring anesthetic and sedation drugs (See WARNINGS/Pediatric Neurotoxicity).

Laboratory Tests

Transient increases in BSP retention, blood glucose and serum creatinine with decrease in BUN, serum cholesterol and alkaline phosphatase have been observed.

Drug Interactions

Isoflurane potentiates the muscle relaxant effect of all muscle relaxants, most notably nondepolarizing muscle relaxants, and MAC (minimum alveolar concentration) is reduced by concomitant administration of N2O. See CLINICAL PHARMACOLOGY.

Carcinogenesis, Mutagenesis, Impairment of Fertility

Carcinogenesis

Swiss ICR mice were given isoflurane to determine whether such exposure might induce neoplasia. Isoflurane was given at 1/2, 1/8 and 1/32 MAC for four in-utero exposures and for 24 exposures to the pups during the first nine weeks of life. The mice were killed at 15 months of age. The incidence of tumors in these mice was the same as in untreated control mice which were given the same background gases, but not the anesthetic.

Mutagenesis

Isoflurane was negative in the in vivo mouse micronucleus and in vitro human lymphocyte chromosomal aberration assay. In published studies, isoflurane was negative in the in vitro bacterial reverse mutation assay (Ames test) in all strains tested (Salmonella typhimurium strains TA98, TA100, and TA1535) in the presence or absence of metabolic activation.

Impairment of Fertility

Male and female Sprague-Dawley rats were exposed to isoflurane at concentrations of 0%, 0.15%, and 0.60% (0, 1/8, and 1/2 MAC) 2 hours per day for 14 consecutive days prior to mating. Isoflurane had no effects on either male or female fertility.

Pregnancy

Risk Summary

There are no adequate and well-controlled studies in pregnant women. In animal reproduction studies, embrofetal toxicity was noted in pregnant mice exposed to 0.075% (increased post implantation losses) and 0.3% isoflurane (increased post implantation losses and decreased live-birth index) during organogenesis.

Published studies in pregnant primates demonstrate that the administration of anesthetic and sedation drugs that block NMDA receptors and/or potentiate GABA activity during the period of peak brain development increases neuronal apoptosis in the developing brain of the offspring when used for longer than 3 hours. There are no data on pregnancy exposures in primates corresponding to periods prior to the third trimester in humans [See Data].

The estimated background risk of major birth defects and miscarriage for the indicated population is unknown. All pregnancies have a background risk of birth defect, loss, or other adverse outcomes. In the U.S. general population, the estimated background risk of major birth defects and miscarriage in clinically recognized pregnancies is 2-4% and 15-20%, respectively.

Data

Animal Data

Pregnant rats were exposed to isoflurane at concentrations of 0%, 0.1%, or 0.4% for two hours per day during organogenesis (Gestational Days 6-15). Isoflurane did not cause malformations or clear maternal toxicity under these conditions.

Pregnant mice exposed to isoflurane at concentrations of 0%, 0.075%, or 0.30% for 2 hours per day during organogenesis (Gestational Days 6-15). Isoflurane increased fetal toxicity (higher post implantation losses at 0.075 and 0.3% groups and significantly lower live-birth index in the 0.3% isoflurane treatment group). Isoflurane did not cause malformations or clear maternal toxicity under these conditions.

Pregnant rats were exposed to concentrations of isoflurane at 0%, 0.1%, or 0.4% for 2 hours per day during late gestation (GD 15-20). Animals appeared slightly sedated during exposure. No adverse effects on the offspring or evidence of maternal toxicity were reported. This study did not evaluate neurobehavioral function including learning and memory in the first generation (F1) of pups.

In a published study in primates, administration of an anesthetic dose of ketamine for 24 hours on Gestation Day 122 increased neuronal apoptosis in the developing brain of the fetus. In other published studies, administration of either isoflurane or propofol for 5 hours on Gestation Day 120 resulted in increased neuronal and oligodendrocyte apoptosis in the developing brain of the offspring. With respect to brain development, this time period corresponds to the third trimester of gestation in the human. The clinical significance of these findings is not clear; however, studies in juvenile animals suggest neuroapoptosis correlates with long-term cognitive deficits (See WARNINGS/ Pediatric Neurotoxicity, PRECAUTIONS/ Pediatric Use, and ANIMAL TOXICOLOGY AND/OR PHARMACOLOGY).

Nursing Mothers

It is not known whether this drug is excreted in human milk. Because many drugs are excreted in human milk, caution should be exercised when isoflurane is administered to a nursing woman.

Pediatric Use

Published juvenile animal studies demonstrate that the administration of anesthetic and sedation drugs, such as isoflurane, that either block NMDA receptors or potentiate the activity of GABA during the period of rapid brain growth or synaptogenesis, results in widespread neuronal and oligodendrocyte cell loss in the developing brain and alterations in synaptic morphology and neurogenesis. Based on comparisons across species, the window of vulnerability to these changes is believed to correlate with exposures in the third trimester of gestation through the first several months of life, but may extend out to approximately 3 years of age in humans.

In primates, exposure to 3 hours of ketamine that produced a light surgical plane of anesthesia did not increase neuronal cell loss, however, treatment regimens of 5 hours or longer of isoflurane increased neuronal cell loss. Data from isoflurane-treated rodents and ketamine-treated primates suggest that the neuronal and oligodendrocyte cell losses are associated with prolonged cognitive deficits in learning and memory. The clinical significance of these nonclinical findings is not known, and healthcare providers should balance the benefits of appropriate anesthesia in pregnant women, neonates, and young children who require procedures with the potential risks suggested by the nonclinical data. (See WARNINGS/ Pediatric Neurotoxicity, PRECAUTIONS/ Pregnancy, and ANIMAL TOXICOLOGY AND/OR PHARMACOLOGY).

ADVERSE REACTIONS

Adverse reactions encountered in the administration of isoflurane are in general dose dependent extensions of pharmacophysiologic effects and include respiratory depression, hypotension and arrhythmias.

Shivering, nausea, vomiting and ileus have been observed in the postoperative period.

As with all other general anesthetics, transient elevations in white blood count have been observed even in the absence of surgical stress. See WARNINGS for information regarding malignant hyperthermia and elevated carboxyhemoglobin levels. During marketing, there have been rare reports of mild, moderate and severe (some fatal) post-operative hepatic dysfunction and hepatitis.

Isoflurane has also been associated with perioperative hyperkalemia (see WARNINGS).

Post-Marketing Events

The following adverse events have been identified during post-approval use of isoflurane, USP. Due to the spontaneous nature of these reports, the actual incidence and relationship of isoflurane, USP to these events cannot be established with certainty.

Cardiac Disorders: Cardiac arrest

Hepatobiliary Disorders: Hepatic necrosis, Hepatic failure.

OVERDOSAGE

In the event of overdosage, or what may appear to be overdosage, the following action should be taken:

Stop drug administration, establish a clear airway and initiate assisted or controlled ventilation with pure oxygen.

DOSAGE AND ADMINISTRATION

Premedication

Premedication should be selected according to the need of the individual patient, taking into account that secretions are weakly stimulated by isoflurane and the heart rate tends to be increased. The use of anticholinergic drugs is a matter of choice.

Inspired Concentration

The concentration of isoflurane being delivered from a vaporizer during anesthesia should be known. This may be accomplished by using:

a) vaporizers calibrated specifically for isoflurane;
b) vaporizers from which delivered flows can be calculated, such as vaporizers delivering a saturated vapor which is then diluted. The delivered concentration from such a vaporizer may be calculated using the formula:

% isoflurane |  | = | 100 PVFV –––––––––
 |  |  | FT(PA-PV)
Where: | PA | = | Pressure of atmosphere
 | PV | = | Vapor pressure of isoflurane
 | FV | = | Flow of gas through vaporizer (mL/min)
 | FT | = | Total gas flow (mL/min)

Isoflurane contains no stabilizer. Nothing in the agent alters calibration or operation of these vaporizers.

Induction

Induction with isoflurane in oxygen or in combination with oxygen-nitrous oxide mixtures may produce coughing, breath holding, or laryngospasm. These difficulties may be avoided by the use of a hypnotic dose of an ultra-short-acting barbiturate. Inspired concentrations of 1.5 to 3.0% isoflurane usually produce surgical anesthesia in 7 to 10 minutes.

Maintenance

Surgical levels of anesthesia may be sustained with a 1.0 to 2.5% concentration when nitrous oxide is used concomitantly. An additional 0.5 to 1.0% may be required when isoflurane is given using oxygen alone. If added relaxation is required, supplemental doses of muscle relaxants may be used.

The level of blood pressure during maintenance is an inverse function of isoflurane concentration in the absence of other complicating problems. Excessive decreases may be due to depth of anesthesia and in such instances may be corrected by lightening anesthesia.

HOW SUPPLIED

Isoflurane, USP is available in unit packages of 100 mL (NDC 12164-012-10) and 250 mL (NDC 12164-012-25) amber colored bottles.

Safety and Handling

Occupational Caution

There is no specific work exposure limit established for isoflurane, USP. However, the National Institute for Occupational Safety and Health Administration (NIOSH) recommends that no worker should be exposed at ceiling concentrations greater than 2 ppm of any halogenated anesthetic agent over a sampling period not to exceed one hour.

The predicted effects of acute overexposure by inhalation of isoflurane, USP include headache, dizziness or (in extreme cases) unconsciousness. There are no documented adverse effects of chronic exposure to halogenated anesthetic vapors (Waste Anesthetic Gases or WAGs) in the workplace. Although results of some epidemiological studies suggest a link between exposure to halogenated anesthetics and increased health problems (particularly spontaneous abortion), the relationship is not conclusive. Since exposure to WAGs is one possible factor in the findings for these studies, operating room personnel, and pregnant women in particular, should minimize exposure. Precautions include adequate general ventilation in the operating room, the use of a well-designed and well-maintained scavenging system, work practices to minimize leaks and spills while the anesthetic agent is in use, and routine equipment maintenance to minimize leaks.

Storage

Store at controlled room temperature 15° - 30°C (59° - 86°F) (see USP). Isoflurane contains no additives and has been demonstrated to be stable at room temperature for a period in excess of five years.

ANIMAL TOXICOLOGY AND/OR PHARMACOLOGY

Published studies in animals demonstrate that the use of anesthetic agents during the period of rapid brain growth or synaptogenesis results in widespread neuronal and oligodendrocyte cell loss in the developing brain and alterations in synaptic morphology and neurogenesis. Based on comparisons across species, the window of vulnerability to these changes is believed to correlate with exposures in the third trimester through the first several months of life, but may extend out to approximately 3 years of age in humans.

In primates, exposure to 3 hours of an anesthetic regimen that produced a light surgical plane of anesthesia did not increase neuronal cell loss, however, treatment regimens of 5 hours or longer increased neuronal cell loss. Data in rodents and in primates suggest that the neuronal and oligodendrocyte cell losses are associated with subtle but prolonged cognitive deficits in learning and memory. The clinical significance of these nonclinical findings is not known, and healthcare providers should balance the benefits of appropriate anesthesia in neonates and young children who require procedures against the potential risks suggested by the nonclinical data. (See WARNINGS/ Pediatric Neurotoxicity and PRECAUTIONS/Pregnancy, Pediatric Use)

Halocarbon Life Sciences, LLC, 1100 Dittman Court, North Augusta, SC 29841

IPN-08
Rev. 02/20

PRINCIPAL DISPLAY PANEL - 250 mL Bottle Label

NDC 12164-012-25
250 mL

Isoflurane, USP

LIQUID FOR INHALATION

A NONFLAMMABLE, NONEXPLOSIVE, INHALATION
ANESTHETIC

Rx ONLY

Halocarbon
LIFE SCIENCES, LLC

1100 Dittman Ct.
North Augusta, SC 29841
www.halocarbon.com